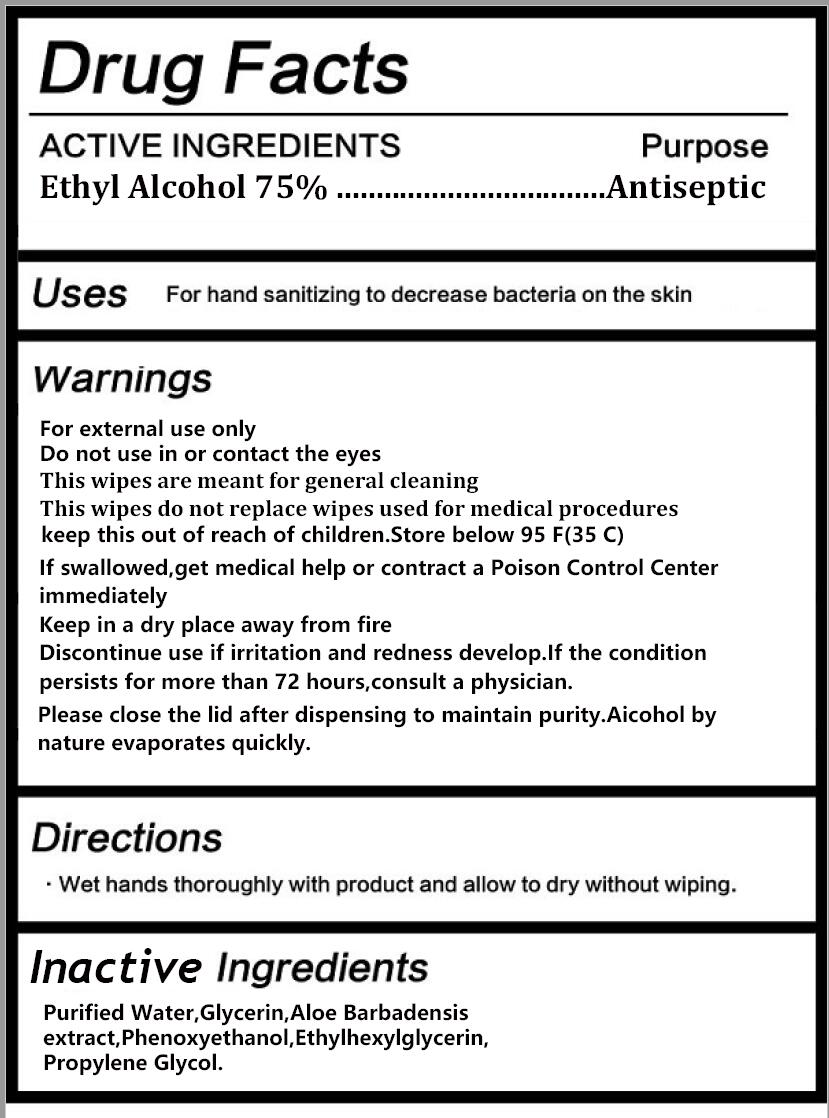 DRUG LABEL: Antibacterial  Wet  Wipes
NDC: 77850-004 | Form: CLOTH
Manufacturer: Zhejiang Aijian Sanitary Products Technology Co., Ltd.
Category: otc | Type: HUMAN OTC DRUG LABEL
Date: 20200806

ACTIVE INGREDIENTS: ALCOHOL 75 g/100 g
INACTIVE INGREDIENTS: PHENOXYETHANOL; ETHYLHEXYLGLYCERIN; PROPYLENE GLYCOL; GLYCERIN; WATER; ALOE VERA LEAF

77850-004 Antibacterial Wet Wipes 75% Alcohol

ACTIVE INGREDIENT

Ethyl Alcohol 75%

PURPOSE

antiseptic

USE

For hand sanitizing to decrease bacteria on the skin

Warning

For external use only
Do not use in or contact the eyes
This wipes are meant for general cleaning
This wipes do not rep lace wipes used for medical procedures
keep this out of reach of children.Store below 95 F(35 C)
If swallowed,get medical help or contract a Poison Control Center
immediately
Keep in a dry place away from fire
Discontinue use if irritation and redness develop.lf the condition
persists for more than 72 hours,consult a physician.
Please close the lid after dispensing to maintain purity Aicohol by
nature evaporates quickly.

Keep this out of reach of children

Directions

. Wet hands thoroughly with product and allow to dry without wiping.

Inactive ingredients

Purified Water,Glycerin,Aloe Barbadensis
extract,Phenoxyethanol,Ethylhexylglycerin,
Propylene Glycol.